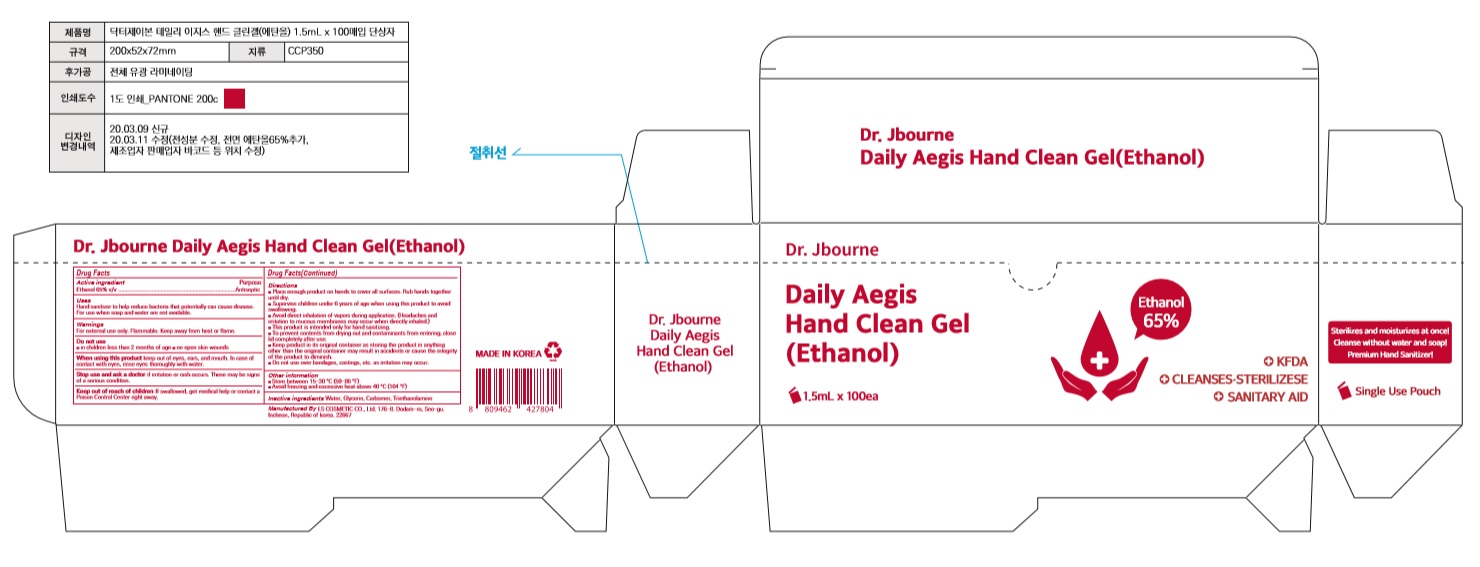 DRUG LABEL: Dr. Jbourne Daily Aegis Hand Clean Gel(Ethanol)
NDC: 59545-0015 | Form: GEL
Manufacturer: LS COSMETIC CO.,LTD.
Category: otc | Type: HUMAN OTC DRUG LABEL
Date: 20200413

ACTIVE INGREDIENTS: ALCOHOL 0.975 mL/1.5 mL
INACTIVE INGREDIENTS: GLYCERIN; CARBOMER HOMOPOLYMER, UNSPECIFIED TYPE; WATER; TROLAMINE

Dr. Jbourne Daily Aegis Hand Clean Gel(Ethanol) 1.5 ml X100 : 59545-0015-1